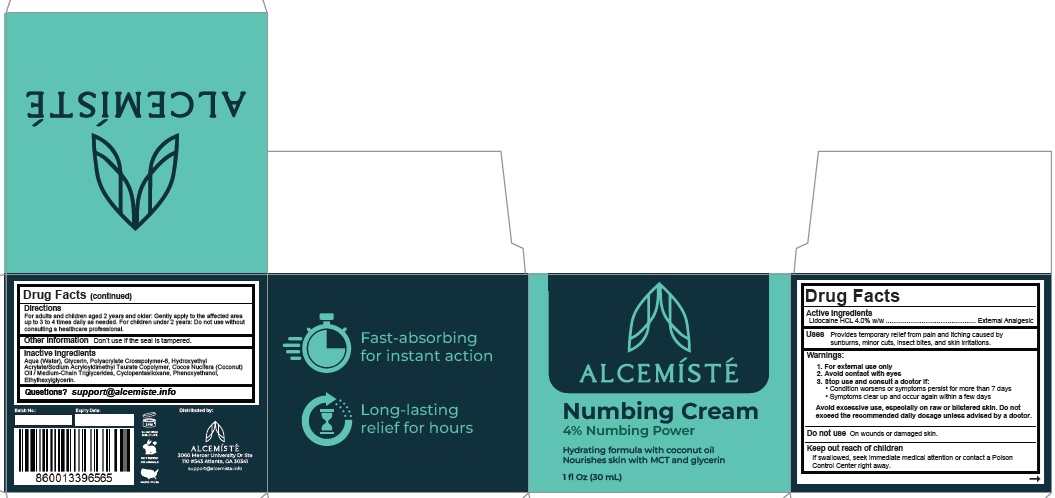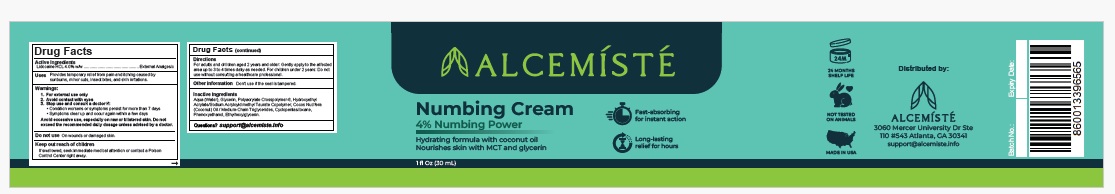 DRUG LABEL: ALCEMISTE
NDC: 87087-001 | Form: CREAM
Manufacturer: Price Team Ventures, LLC
Category: otc | Type: HUMAN OTC DRUG LABEL
Date: 20250905

ACTIVE INGREDIENTS: LIDOCAINE HYDROCHLORIDE 4 g/100 mL
INACTIVE INGREDIENTS: WATER; ISOPROPYL MYRISTATE; GLYCERIN; ETHOXYDIGLYCOL; POLYACRYLATE CROSSPOLYMER-6; CYCLOPENTASILOXANE; POLYSORBATE 60; PHENOXYETHANOL; ETHYLHEXYLGLYCERIN; XANTHAN GUM

Active Ingredient

Lidocaine HCL 4%

Purpose

External Analgesic

Uses

Provides temporary relief from pain and itching caused by sunburns, minor cuts, insect bites, and skin irritations.

Warnings

1. For external use only
2. Avoid contact with the eyes
3. Stop use and consult a doctor if:

- Condition worsens or symptoms persist for more than 7 days
- Symptoms clear up and occur again within a few days

Avoid excessive use, especially on raw or blistered skin. Do not
exceed the recommended daily dosage unless advised by a doctor.

Do not useon wounds or damaged skin.

Keep out of reach of children.
If swallowed, seek immediate medical attention or contact a Poison Control Center right away.

Directions

For adults and children aged 2 years and older: Gently apply to the affected area. Up to 3 to 4 times daily as needed.

For children under 2 years: Do not use without consulting a healthcare professional.

Other information

Don’t use if the seal is tampered.

Inactive Ingredients

Agua (Water), Isopropyl myristate , Glycerin, Ethoxydiglycol , Polyacrylate, Crosspolymer-6, Cyclopentasiloxane, Polysorbate, Phenoxyethanol , Ethylhexylglycerin, Xanthan Gum